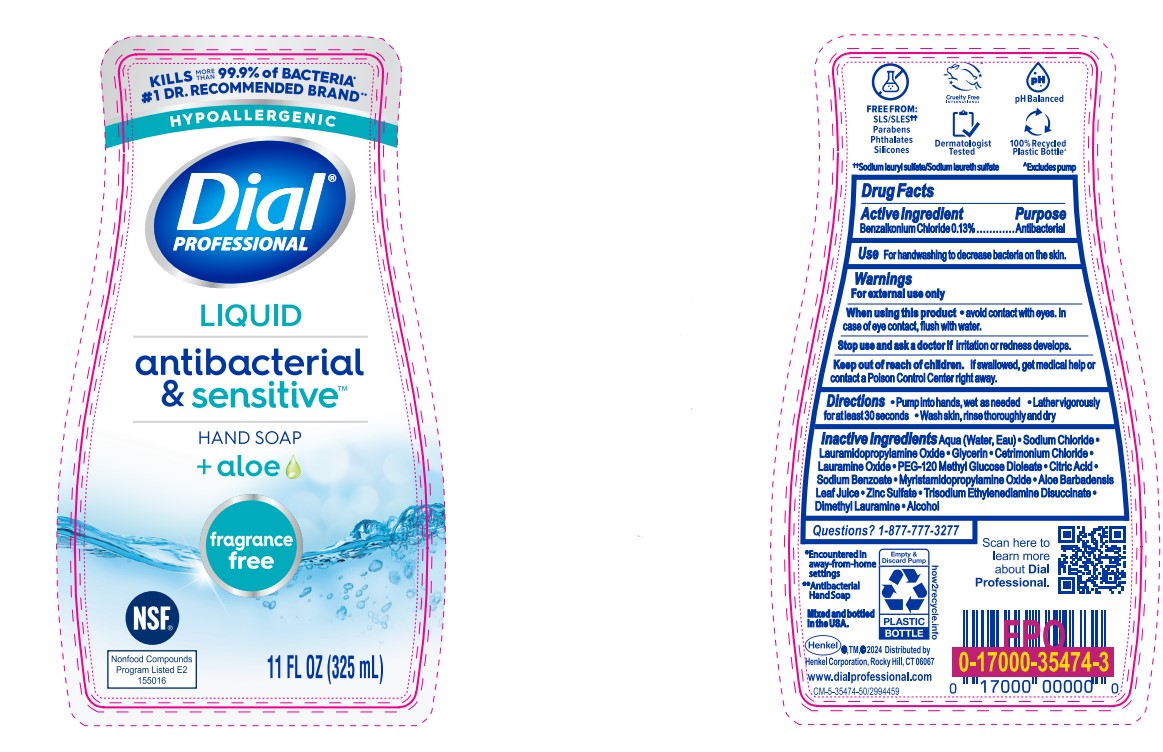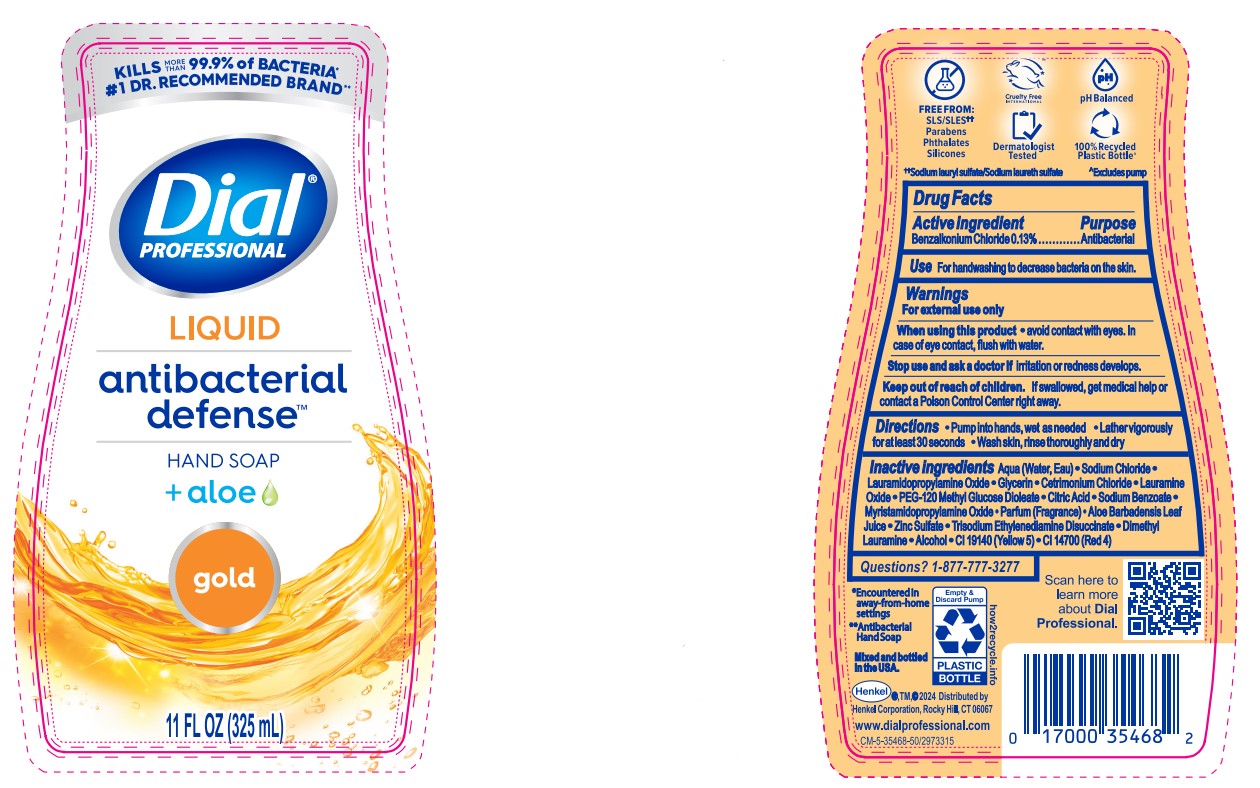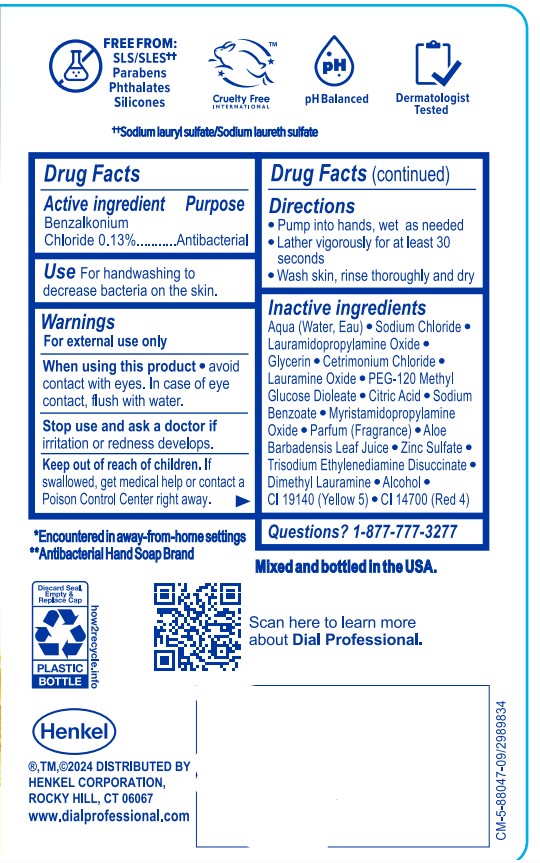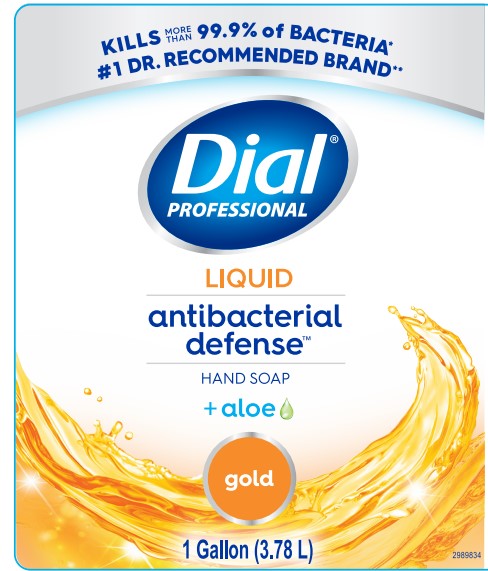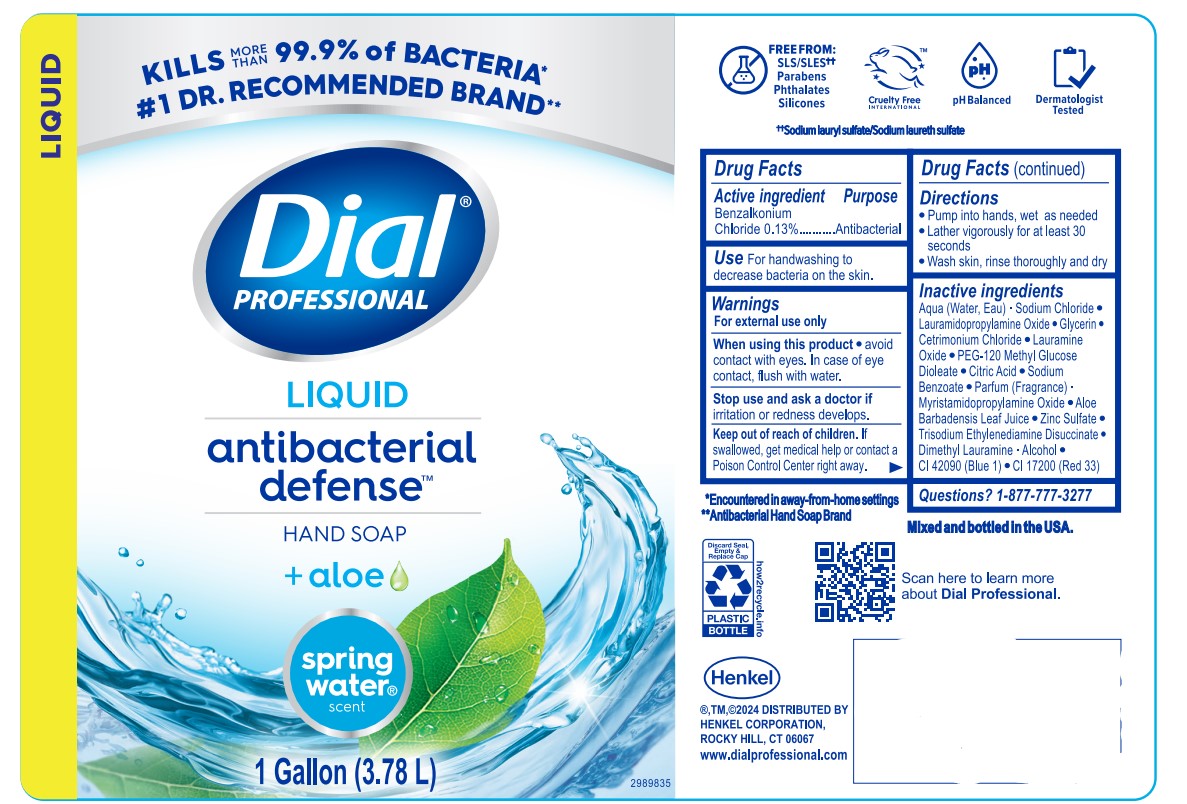 DRUG LABEL: Dial Professional Antibacterial Defense Spring Water
NDC: 54340-121 | Form: SOLUTION
Manufacturer: Henkel Corporation
Category: otc | Type: HUMAN OTC DRUG LABEL
Date: 20251209

ACTIVE INGREDIENTS: BENZALKONIUM CHLORIDE 0.13 g/100 mL
INACTIVE INGREDIENTS: ZINC SULFATE 0.05 g/100 mL; ALCOHOL 0.013 g/100 mL; LAURAMIDOPROPYLAMINE OXIDE 1.635 g/100 mL; MYRISTAMIDOPROPYLAMINE OXIDE 0.19 g/100 mL; TRISODIUM ETHYLENEDIAMINE DISUCCINATE 0.0185 g/100 mL; DIMETHYL LAURAMINE 0.0162 g/100 mL; LAURAMINE OXIDE 0.975 g/100 mL; CITRIC ACID MONOHYDRATE 0.575 g/100 mL; WATER 89.65 mL/100 mL; ALOE VERA LEAF 0.0997 g/100 mL; CETRIMONIUM CHLORIDE 1.5 g/100 mL; SODIUM BENZOATE 0.4 g/100 mL; GLYCERIN 1.5 g/100 mL; PEG-120 METHYL GLUCOSE DIOLEATE 0.75 g/100 mL; SODIUM CHLORIDE 2.2 g/100 mL; FD&C BLUE NO. 1 0.000051 g/100 mL; D&C RED NO. 33 0.000017 g/100 mL

Dial Professional Gold Antibacterial Liquid Hand Soap
Dial Professional Antibacterial Gold Liquid Hand Soap Refill for Versa Dispenser
Dial Professional Liquid Antibaterial Defense Hand Soap Spring Water Scent
Dial Professional Liquid Antibaterial Defense Hand Soap Gold
Dial Professional Liquid Antibaterial& Sensitive Hand Soap Fragrance Free

Active Ingredient

Benzalkonium Chloride 0.13%

Purpose

Antibacterial

Uses

For Handwashing to decreases bacteria on the skin.

Warnings

For external use only.

When Using this Product

Avoid Contact with eyes. In case of eye contact, flush with water.

Stop use and ask doctor if

Irritation or redness develops

Keep out of reach of children.

If swallowed get medical help or contact a Poison Control Center right away.

Directions

- Pump into hands, wet as needed.
- Lather vigorously for at least 30 seconds.
- Wash skin, rinse thoroughly and dry.

Inactive Ingredients

Variant Gold:

Inactive ingredients: Aqua (Water, Eau) · Sodium Chloride · Lauramidopropylamine Oxide · Glycerin · Cetrimonium Chloride · Lauramine Oxide · PEG-120 Methyl Glucose Dioleate · Citric Acid · Sodium Benzoate · Myristamidopropylamine Oxide · Parfum (Fragrance) · Aloe Barbadensis Leaf Juice · Zinc Sulfate · Trisodium Ethylenediamine Disuccinate · Dimethyl Lauramine. Alcohol. CI 19140 (yellow 5). CI 14700 (Red 4)

Variant AB Fragrance Free:

Inactive ingredients: Aqua (Water, Eau) · Sodium Chloride · Lauramidopropylamine Oxide · Glycerin · Cetrimonium Chloride · Lauramine Oxide ·
PEG-120 Methyl Glucose Dioleate · Citric Acid · Sodium Benzoate · Myristamidopropylamine Oxide · Aloe Barbadensis Leaf Juice · Zinc Sulfate · Trisodium Ethylenediamine Disuccinate · Dimethyl Lauramine · Alcohol

Variant Spring Water:

Inactive ingredients: Aqua (Water, Eau) · Sodium Chloride · Lauramidopropylamine Oxide · Glycerin · Cetrimonium Chloride · Lauramine Oxide ·
PEG-120 Methyl Glucose Dioleate · Citric Acid · Sodium Benzoate · Parfum (Fragrance) · Myristamidopropylamine Oxide · Aloe Barbadensis Leaf Juice · Zinc Sulfate · Trisodium Ethylenediamine Disuccinate · Dimethyl Lauramine · Alcohol · CI 42090 (Blue 1) · CI 17200 (Red 33)

Questions

Questions? 1-877-777-3277

Legal Entity

henkel Bean Logo

R,TM,c2024 Distributed by

Henkel Corporation,Rocky Hill, CT 06067

www.dialsprofessional.com

^Encountered in household settings

#Antibacterial Hand Soap

Indications & Usage

For handwasing to decrease bacteria on the skin.

Topical Liquid

Liquid Hand Soap